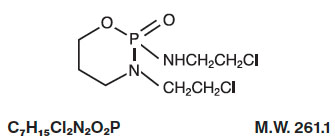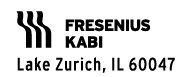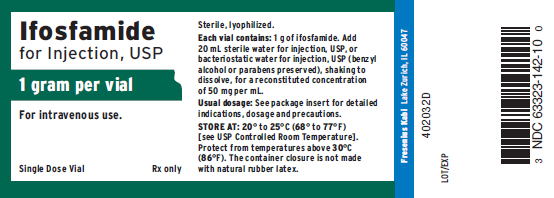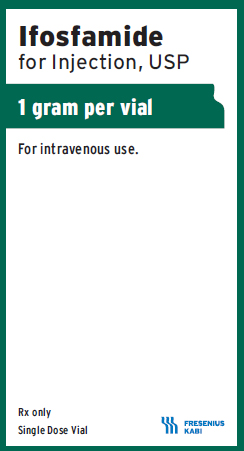 DRUG LABEL: Ifosfamide
NDC: 63323-142 | Form: INJECTION, POWDER, LYOPHILIZED, FOR SOLUTION
Manufacturer: Fresenius Kabi USA, LLC
Category: prescription | Type: HUMAN PRESCRIPTION DRUG LABEL
Date: 20241014

ACTIVE INGREDIENTS: IFOSFAMIDE 1 g/1 1
INACTIVE INGREDIENTS: BENZYL ALCOHOL

HIGHLIGHTS OF PRESCRIBING INFORMATION

These highlights do not include all the information needed to use IFOSFAMIDE FOR INJECTION safely and effectively. See full prescribing information for IFOSFAMIDE FOR INJECTION.
IFOSFAMIDE for injection, intravenous use
Initial U.S. Approval: 1988

WARNING: MYELOSUPPRESSION, NEUROTOXICITY, and UROTOXICITY

See full prescribing information for complete boxed warning.

- Myelosuppression can be severe and lead to fatal infections (5.1)
- CNS toxicities can be severe and result in encephalopathy and death (5.2)
- Nephrotoxicity can be severe and result in renal failure. Hemorrhagic cystitis can be severe. (5.3)

1 INDICATIONS AND USAGE

Ifosfamide for Injection is an alkylating drug indicated for use in combination with certain other approved antineoplastic agents for third-line chemotherapy of germ cell testicular cancer. It should be used in combination with mesna for prophylaxis of hemorrhagic cystitis. (1)

2 DOSAGE AND ADMINISTRATION

Dosage and duration of treatment and/or treatment intervals depend on the scheme of combination therapy, the patient’s general state of health and organ function, and the results of laboratory monitoring. (2)

- Ifosfamide for Injection should be administered as a slow intravenous infusion lasting a minimum of 30 minutes at a dose of 1.2 grams per m^2 per day for 5 consecutive days. (2)
- Treatment is repeated every 3 weeks or after recovery from hematologic toxicity. (2)
- To prevent bladder toxicity, Ifosfamide for Injection should be given with extensive hydration consisting of at least 2 liters of oral or intravenous fluid per day. (2, 5.3)
- Mesna should be used to reduce the incidence of hemorrhagic cystitis. (2)

3 DOSAGE FORMS AND STRENGTHS

- Single dose vials: 1 gram, 3 grams (3)

4 CONTRAINDICATIONS

- Known hypersensitivity to administration of ifosfamide. (4)
- Urinary outflow obstruction. (4)

5 WARNINGS AND PRECAUTIONS

- Myelosuppression: Can be severe and lead to fatal infections. Monitor blood counts prior to and at intervals after treatment. (5.1)
- Neurotoxicity: Severe and fatal neurotoxicity can occur. Carefully monitor the patient for CNS toxicity and other neurotoxic effects. Discontinue therapy should encephalopathy develop. (5.2)
- Urotoxicity: Severe nephrotoxicity with renal failure and death can occur. Monitor for nephrotoxicity with serum and urine chemistries. Mesna should be used to reduce hemorrhagic cystitis. (5.3)
- Cardiotoxicity: Arrhythmias, other ECG changes, and cardiomyopathy can occur and result in death. Use with caution in patients with cardiac risk factors and in patients with preexisting cardiac disease. The risk of cardiotoxicity is dose dependent. (5.4)
- Pulmonary toxicity: Interstitial pneumonitis, pulmonary fibrosis, and other forms of pulmonary toxicity with fatal outcomes can occur. Monitor for signs and symptoms of pulmonary toxicity and treat as clinically indicated (5.5)
- Secondary malignancies as late sequelae have occurred. (5.6)
- Pregnancy: Can cause fetal harm. Women should not become pregnant and men should not father a child during therapy. (5.8)
- Anaphylactic/anaphylactoid reactions have been reported. (5.10)

6 ADVERSE REACTIONS

In clinical trials of ifosfamide monotherapy, the most common (≥ 10%) adverse reactions were alopecia, nausea/vomiting, leukopenia, anemia, CNS toxicity, hematuria, and infection. (6.1)

To report SUSPECTED ADVERSE REACTIONS, contact Fresenius Kabi USA, LLC at 1-800-551-7176 or FDA at 1-800-FDA-1088 or www.fda.gov/medwatch.

7 DRUG INTERACTIONS

- CYP3A4 Inducers: monitor for increased toxicity when used in combination with CYP3A4 inducers. (7.1)
- CYP3A4 Inhibitors: use in combination with CYP3A4 inhibitors could decrease the effectiveness of ifosfamide. (7.2)

8 USE IN SPECIFIC POPULATIONS

- Pregnancy: fetal growth retardation and neonatal anemia. (8.1)
- Geriatric use: dose selection should be cautious. (8.5)
- Patients with renal impairment: monitor for toxicity and consider dose reduction as needed (8.6)

FULL PRESCRIBING INFORMATION

WARNING: MYELOSUPPRESSION, NEUROTOXICITY, and UROTOXICITY

Myelosuppression can be severe and lead to fatal infections. Monitor blood counts prior to and at intervals after each treatment cycle. CNS toxicities can be severe and result in encephalopathy and death. Monitor for CNS toxicity and discontinue treatment for encephalopathy. Nephrotoxicity can be severe and result in renal failure. Hemorrhagic cystitis can be severe and can be reduced by the prophylactic use of mesna. [see Warnings and Precautions (5.1-5.3)]

1 INDICATIONS AND USAGE

Ifosfamide for Injection is indicated for use in combination with certain other approved antineoplastic agents for third-line chemotherapy of germ cell testicular cancer. It should be used in combination with mesna for prophylaxis of hemorrhagic cystitis.

2 DOSAGE AND ADMINISTRATION

Ifosfamide for Injection should be administered intravenously at a dose of 1.2 grams per m^2 per day for 5 consecutive days. Treatment is repeated every 3 weeks or after recovery from hematologic toxicity.

In order to prevent bladder toxicity, Ifosfamide for Injection should be given with extensive hydration consisting of at least 2 liters of oral or intravenous fluid per day. Mesna should be used to reduce the incidence of hemorrhagic cystitis. Ifosfamide for Injection should be administered as a slow intravenous infusion lasting a minimum of 30 minutes. Studies of Ifosfamide for Injection in patients with hepatic or renal impairment have not been conducted [see Use in Specific Populations (8.6, 8.7)].

Injections are prepared for parenteral use by adding Sterile Water for Injection, USP or Bacteriostatic Water for Injection, USP (benzyl alcohol or parabens preserved), to the vial and shaking to dissolve. Before parenteral administration, the substance must be completely dissolved. Use the quantity of diluents shown below to constitute the product:

Dosage Strength | Quantity of Diluent | Final Concentration
1 gram | 20 mL | 50 mg per mL
3 grams | 60 mL | 50 mg per mL

Solutions of ifosfamide may be diluted further to achieve concentrations of 0.6 to 20 mg/mL in the following fluids:
5% Dextrose Injection, USP
0.9% Sodium Chloride Injection, USP
Lactated Ringer’s Injection, USP
Sterile Water for Injection, USP

Because essentially identical stability results were obtained for Sterile Water admixtures as for the other admixtures (5% Dextrose Injection, 0.9% Sodium Chloride Injection, and Lactated Ringer’s Injection), the use of large volume parenteral glass bottles, VIAFLEX bags or PAB bags that contain intermediate concentrations or mixtures of excipients (e.g., 2.5% Dextrose Injection, 0.45% Sodium Chloride Injection, or 5% Dextrose and 0.9% Sodium Chloride Injection) is also acceptable.

Constituted or constituted and further diluted solutions of Ifosfamide for Injection should be refrigerated and used within 24 hours. Benzyl-alcohol-containing solutions can reduce the stability of ifosfamide.

Parenteral drug products should be inspected visually for particulate matter and discoloration prior to administration, whenever solution and container permit.

3 DOSAGE FORMS AND STRENGTHS

1 gram single-dose vial
3 gram single-dose vial

4 CONTRAINDICATIONS

Ifosfamide for Injection is contraindicated in patients with:

- Known hypersensitivity to administration of ifosfamide.
- Urinary outflow obstruction.

5 WARNINGS AND PRECAUTIONS

5.1 Myelosuppression, Immunosuppression, and Infections

Treatment with ifosfamide may cause myelosuppression and significant suppression of immune responses, which can lead to severe infections. Fatal outcomes of ifosfamide-associated myelosuppression have been reported. Ifosfamide-induced myelosuppression can cause leukopenia, neutropenia, thrombocytopenia (associated with a higher risk of bleeding events), and anemia. The nadir of the leukocyte count tends to be reached approximately during the second week after administration. When Ifosfamide for Injection is given in combination with other chemotherapeutic/hematotoxic agents and/or radiation therapy, severe myelosuppression is frequently observed. The risk of myelosuppression is dose-dependent and is increased with administration of a single high dose compared with fractionated administration. The risk of myelosuppression is also increased in patients with reduced renal function.

Severe immunosuppression has led to serious, sometimes fatal, infections. Sepsis and septic shock also have been reported. Infections reported with ifosfamide include pneumonias, as well as other bacterial, fungal, viral, and parasitic infections. Latent infections can be reactivated. In patients treated with ifosfamide, reactivation has been reported for various viral infections. Infections must be treated appropriately. Antimicrobial prophylaxis may be indicated in certain cases of neutropenia at the discretion of the managing physician. In case of neutropenic fever, antibiotics and/or antimycotics must be given. Close hematologic monitoring is recommended. White blood cell (WBC) count, platelet count and hemoglobin should be obtained prior to each administration and at appropriate intervals after administration. Unless clinically essential, Ifosfamide for Injection should not be given to patients with a WBC count below 2,000/µL and/or a platelet count below 50,000/µL.

Ifosfamide for Injection should be given cautiously, if at all, to patients with presence of an infection, severe immunosuppression or compromised bone marrow reserve, as indicated by leukopenia, granulocytopenia, extensive bone marrow metastases, prior radiation therapy, or prior therapy with other cytotoxic agents.

5.2 Central Nervous System Toxicity, Neurotoxicity

Administration of ifosfamide can cause CNS toxicity and other neurotoxic effects. The risk of CNS toxicity and other neurotoxic effects necessitates careful monitoring of the patient. Neurologic manifestations consisting of somnolence, confusion, hallucinations, blurred vision, psychotic behavior, extrapyramidal symptoms, urinary incontinence, seizures, and in some instances, coma, have been reported following Ifosfamide for Injection therapy. There have also been reports of peripheral neuropathy associated with ifosfamide use.

Ifosfamide neurotoxicity may become manifest within a few hours to a few days after first administration and in most cases resolves within 48 to 72 hours of ifosfamide discontinuation. Symptoms may persist for longer periods of time. Supportive therapy should be maintained until their complete resolution. Occasionally, recovery has been incomplete. Fatal outcomes of CNS toxicity have been reported. Recurrence of CNS toxicity after several uneventful treatment courses has been reported. If encephalopathy develops, administration of ifosfamide should be discontinued.

Due to the potential for additive effects, drugs acting on the CNS (such as antiemetics, sedatives, narcotics, or antihistamines) must be used with particular caution or, if necessary, be discontinued in case of ifosfamide-induced encephalopathy.

Manifestations of CNS toxicity may impair a patient’s ability to operate an automobile or other heavy machinery.

5.3 Renal and Urothelial Toxicity and Effects

Ifosfamide is both nephrotoxic and urotoxic. Glomerular and tubular kidney function must be evaluated before commencement of therapy as well as during and after treatment. Monitor urinary sediment regularly for the presence of erythrocytes and other signs of uro/nephrotoxicity.

Monitor serum and urine chemistries, including phosphorus and potassium regularly. Administer appropriate replacement therapy as indicated. Renal parenchymal and tubular necrosis have been reported in patients treated with ifosfamide. Acute tubular necrosis, acute renal failure, and chronic renal failure secondary to ifosfamide therapy have been reported, and fatal outcome from nephrotoxicity has been documented.

Disorders of renal function, (glomerular and tubular) following ifosfamide administration are very common. Manifestations include a decrease in glomerular filtration rate, increased serum creatinine, proteinuria, enzymuria, cylindruria, aminoaciduria, phosphaturia, and glycosuria as well as tubular acidosis. Fanconi syndrome, renal rickets, and growth retardation in children as well as osteomalacia in adults also have been reported. Development of a syndrome resembling SIADH (syndrome of inappropriate antidiuretic hormone secretion) has been reported with ifosfamide.

Tubular damage may become apparent during therapy, months or even years after cessation of treatment. Glomerular or tubular dysfunction may resolve with time, remain stable, or progress over a period of months or years, even after completion of ifosfamide treatment.

The risk and expected benefits of ifosfamide therapy should be carefully weighed when considering the use of ifosfamide in patients with preexisting renal impairment or reduced nephron reserve.

Urotoxic side effects, especially hemorrhagic cystitis, have been very commonly associated with the use of Ifosfamide for Injection. These urotoxic effects can be reduced by prophylactic use of mesna.
Hemorrhagic cystitis requiring blood transfusion has been reported with ifosfamide. The risk of hemorrhagic cystitis is dose-dependent and increased with administration of single high doses compared to fractionated administration. Hemorrhagic cystitis after a single dose of ifosfamide has been reported. Past or concomitant radiation of the bladder or busulfan treatment may increase the risk for hemorrhagic cystitis.

Before starting treatment, it is necessary to exclude or correct any urinary tract obstructions [see Contraindications (4)].

During or immediately after administration, adequate amounts of fluid should be ingested or infused to force dieresis in order to reduce the risk of urinary tract toxicity. Obtain a urinalysis prior to each dose of Ifosfamide for Injection. If microscopic hematuria (greater than 10 RBCs per high power field) is present, then subsequent administration should be withheld until complete resolution. Further administration of Ifosfamide for Injection should be given with vigorous oral or parenteral hydration.

Ifosfamide should be used with caution, if at all, in patients with active urinary tract infections.

5.4 Cardiotoxicity

Manifestations of cardiotoxicity reported with ifosfamide treatment include:
- Supraventricular or ventricular arrhythmias, including atrial/supraventricular tachycardia, atrial fibrillation, pulseless ventricular tachycardia
- Decreased QRS voltage and ST-segment or T-wave changes
- Toxic cardiomyopathy leading to heart failure with congestion and hypotension
- Pericardial effusion, fibrinous pericarditis, and epicardial fibrosis

Fatal outcome of ifosfamide-associated cardiotoxicity has been reported.

The risk of developing cardiotoxic effects is dose-dependent. It is increased in patients with prior or concomitant treatment with other cardiotoxic agents or radiation of the cardiac region and, possibly, renal impairment.

Particular caution should be exercised when ifosfamide is used in patients with risk factors for cardiotoxicity and in patients with preexisting cardiac disease.

5.5 Pulmonary Toxicity

Interstitial pneumonitis, pulmonary fibrosis, and other forms of pulmonary toxicity have been reported with ifosfamide treatment. Pulmonary toxicity leading to respiratory failure as well as fatal outcome has also been reported. Monitor for signs and symptoms of pulmonary toxicity and treat as clinically indicated.

5.6 Secondary Malignancies

Treatment with ifosfamide involves the risk of secondary tumors and their precursors as late sequelae. The risk of myelodysplastic alterations, some progressing to acute leukemias, is increased. Other malignancies reported after use of ifosfamide or regimens with ifosfamide include lymphoma, thyroid cancer, and sarcomas.

The secondary malignancy may develop several years after chemotherapy has been discontinued.

5.7 Veno-occlusive Liver Disease

Veno-occlusive liver disease has been reported with chemotherapy that included ifosfamide.

5.8 Pregnancy

Ifosfamide for Injection can cause fetal harm when administered to a pregnant woman. Fetal growth retardation and neonatal anemia have been reported following exposure to ifosfamide-containing chemotherapy regimens during pregnancy. Ifosfamide is genotoxic and mutagenic in male and female germ cells. Embryotoxic and teratogenic effects have been observed in mice, rats and rabbits at doses 0.05 to 0.075 times the human dose.

Women should not become pregnant and men should not father a child during therapy with ifosfamide. Further, men should not father a child for up to 6 months after the end of therapy. If this drug is used during pregnancy, or if the patient becomes pregnant while taking this drug or after treatment, the patient should be apprised of the potential hazard to a fetus [see Use in Specific Populations (8.1)].

5.9 Effects on Fertility

Ifosfamide interferes with oogenesis and spermatogenesis. Amenorrhea, azoospermia, and sterility in both sexes have been reported. Development of sterility appears to depend on the dose of ifosfamide, duration of therapy, and state of gonadal function at the time of treatment. Sterility may be irreversible in some patients.

Female Patients
Amenorrhea has been reported in patients treated with ifosfamide. The risk of permanent chemotherapy-induced amenorrhea increases with age. Pediatric patients treated with ifosfamide during prepubescence subsequently may not conceive and those who retain ovarian function after completing treatment are at increased risk of developing premature menopause.

Male Patients
Men treated with ifosfamide may develop oligospermia or azoospermia. Pediatric patients treated with ifosfamide during prepubescence might not develop secondary sexual characteristics normally, but may have oligospermia or azoospermia. Azoospermia may be reversible in some patients, though the reversibility may not occur for several years after cessation of therapy. Sexual function and libido are generally unimpaired in these patients. Some degree of testicular atrophy may occur. Patients treated with ifosfamide have subsequently fathered children.

5.10 Anaphylactic/Anaphylactoid Reactions and Cross-sensitivity

Anaphylactic/anaphylactoid reactions have been reported in association with ifosfamide. Cross-sensitivity between oxazaphosphorine cytotoxic agents has been reported.

5.11 Impairment of Wound Healing

Ifosfamide may interfere with normal wound healing.

5.12 Nursing

Ifosfamide is excreted in breast milk. Women must not breastfeed during treatment with ifosfamide [see Use in Specific Populations (8.3)].

6 ADVERSE REACTIONS

6.1 Adverse Reactions from Clinical Trials

Because clinical trials are conducted under widely varying conditions, adverse reaction rates observed in the clinical trials of a drug cannot be directly compared to rates in the clinical trials of another drug and may not reflect the rates observed in clinical practice. The adverse reactions and frequencies below are based on 30 publications describing clinical experience with fractionated administration of ifosfamide as monotherapy with a total dose of 4 to 12 g/m^2 per course.

System Organ Class (SOC) | Adverse Reaction | Percentage (Ratio)
INFECTIONS AND INFESTATIONS | Infection | 9.9% (112/1128)
BLOOD AND LYMPHATIC SYSTEM DISORDERS | Leukopenia^1 (any) | -1a
BLOOD AND LYMPHATIC SYSTEM DISORDERS | Leukopenia <1 x 10^3/µL | 43.5% (267/614)
BLOOD AND LYMPHATIC SYSTEM DISORDERS | Thrombocytopenia^2 (any) | -2a
BLOOD AND LYMPHATIC SYSTEM DISORDERS | Thrombocytopenia, 50 x 10^3/µL | 4.8% (35/729)
BLOOD AND LYMPHATIC SYSTEM DISORDERS | Anemia^3 | 37.9% (202/533)
METABOLISM AND NUTRITION DISORDERS | Anorexia | 1.1% (15/1317)
NERVOUS SYSTEM DISORDERS | Central nervous system toxicity^4,5 | 15.4% (154/1001)
NERVOUS SYSTEM DISORDERS | Peripheral neuropathy | 0.4% (5/1317)
CARDIAC DISORDERS | Cardiotoxicity^6 | 0.5% (7/1317)
VASCULAR DISORDERS | Hypotension^7 | 0.3% (4/1317)
GASTROINTESTINAL DISORDERS | Nausea/Vomiting | 46.8% (443/964)
GASTROINTESTINAL DISORDERS | Diarrhea | 0.7% (9/1317)
GASTROINTESTINAL DISORDERS | Stomatitis | 0.3% (4/1317)
HEPATOBILIARY DISORDERS | Hepatotoxicity^8 | 1.8% (22/1190)
SKIN AND SUBCUTANEOUS TISSUES DISORDERS | Alopecia | 89.6% (540/603)
SKIN AND SUBCUTANEOUS TISSUES DISORDERS | Dermatitis | 0.08% (1/1317)
SKIN AND SUBCUTANEOUS TISSUES DISORDERS | Papular rash | 0.08% (1/1317)
RENAL AND URINARY DISORDERS | Hemorrhagic cystitis | -^9
RENAL AND URINARY DISORDERS | Hematuria
RENAL AND URINARY DISORDERS | - without mesna | 44.1% (282/640)
RENAL AND URINARY DISORDERS | - with mesna | 21.3% (33/155)
RENAL AND URINARY DISORDERS | Macrohematuria
RENAL AND URINARY DISORDERS | - without mesna | 11.1% (66/594)
RENAL AND URINARY DISORDERS | - with mesna | 5.2% (5/97)
RENAL AND URINARY DISORDERS | Renal dysfunction^10 | -
RENAL AND URINARY DISORDERS | Renal structural damage | -
GENERAL DISORDERS AND ADMINISTRATIVE SITE CONDITIONS | Phlebitis^11 | 2.8% (37/1317)
GENERAL DISORDERS AND ADMINISTRATIVE SITE CONDITIONS | Neutropenic fever^12 | 1.0% (13/1317)
GENERAL DISORDERS AND ADMINISTRATIVE SITE CONDITIONS | Fatigue | 0.3% (4/1317)
GENERAL DISORDERS AND ADMINISTRATIVE SITE CONDITIONS | Malaise | Unable to calculate

^1 The following adverse reaction terms have been reported for leukopenia: neutropenia, granulocytopenia, lymphopenia, and pancytopenia. For neutropenic fever, see below.
1a The frequency category of leukopenia is based on the frequency of leukopenia <3 x 10^3/µL [42.5% (150/353) not shown in table] and <1 x 10^3/µL; a relevant percentage ratio cannot be calculated for the pooled data and thus the conservative frequency category of “Very common” was included in the table.
^2 Thrombocytopenia may also be complicated by bleeding. Bleeding with fatal outcome has been reported.
2a Frequency of thrombocytopenia is based on the frequency of thrombocytopenia <100 x 10^3/µL [12.2% (24/196) not shown in table] and <50 x 10^3/µL; a relevant percentage ratio cannot be calculated from the pooled data and thus the conservative frequency of “Very common” was included in the table.
^3 Includes cases reported as anemia and decrease in hemoglobin/hematocrit.
^4 Encephalopathy with coma and death has been reported.
^5 Central nervous system toxicity was reported to be manifested by the following signs and symptoms: Abnormal behavior, Affect lability Aggression, Agitation, Anxiety, Aphasia, Asthenia, Ataxia, Cerebellar syndrome, Cerebral function deficiency,
Cognitive disorder, Coma, Confusional state, Convulsions, Cranial nerve dysfunction, Depressed state of consciousness, Depression, Disorientation, Dizziness, Electroencephalogram abnormal, Encephalopathy, Flat affect. Hallucinations, Headache, Ideation, Lethargy, Memory impairment, Mood change, Motor dysfunction, Muscle spasms, Myoclonus, Progressive loss of brainstem reflexes, Psychotic reaction, Restlessness, Somnolence, Tremor, Urinary incontinence.
^6 Cardiotoxicity was reported as congestive heart failure, tachycardia, pulmonary edema. Fatal outcome has been reported.
^7 Hypotension leading to shock and fatal outcome has been reported.
^8 Hepatotoxicity was reported as increases in liver enzymes, i.e., serum alanine aminotransferase, serum aspartate aminotransferase, alkaline phosphatase, gamma-glutamyltransferase and lactate dehydrogenase, increased bilirubin, jaundice, hepatorenal syndrome.
^9 Frequency of hemorrhagic cystitis is estimated based on the frequency of hematuria. Reported symptoms of hemorrhagic cystitis included dysuria and pollakiuria. See also Post-marketing Adverse Reactions (6.2).
^10 Renal dysfunction was reported to be manifested as: Renal failure (including acute renal failure, irreversible renal failure; fatal outcomes have been reported), Serum creatinine increased, BUN increased, Creatinine clearance decreased, Metabolic acidosis, Anuria, Oliguria, Glycosuria, Hyponatremia, Uremia, Creatinine clearance increased. Renal structural damage was reported to be manifested as: Acute tubular necrosis, renal parenchymal damage, Enzymuria, Cylindruria, Proteinuria.
^11 Includes cases reported as phlebitis and irritation of the venous walls.
^12 Frequency of neutropenic fever: Includes cases reported as granulocytopenic fever.

6.2 Postmarketing Experience

The following adverse reactions have been identified during post-approval use of ifosfamide. Because these reactions are reported voluntarily from a population of uncertain size, it is not always possible to reliably estimate their frequency or establish a causal relationship to drug exposure.

INFECTIONS AND INFESTATIONS:
The following manifestations have been associated with myelosuppression and immunosuppression caused by ifosfamide: increased risk for and severity of infections†, pneumonias†, sepsis and septic shock (including fatal outcomes), as well as reactivation of latent infections, including viral hepatitis†, Pneumocystis jiroveci†, herpes zoster, Strongyloides, progressive multifocal leukoencephalopathy†, and other viral and fungal infections.

† Severe immunosuppression has led to serious, sometimes fatal, infections.

NEOPLASMS, BENIGN AND MALIGNANT AND UNSPECIFIED (INCL CYSTS AND POLYPS):
As treatment-related secondary malignancy*, Acute leukemia* (Acute myeloid leukemia)*, Acute promyelocytic leukemia*, Acute lymphocytic leukemia*, Myelodysplastic syndrome, Lymphoma (Non-Hodgkin’s lymphoma), Sarcomas*, Renal cell carcinoma, Thyroid cancer

BLOOD AND LYMPHATIC SYSTEM DISORDERS:
Hematotoxicity*, Myelosuppression manifested as Bone marrow failure, Agranulocytosis; Febrile bone marrow aplasia; Disseminated intravascular coagulation, Hemolytic uremic syndrome, Hemolytic anemia, Neonatal anemia, Methemoglobinemia

IMMUNE SYSTEM DISORDERS:
Angioedema*, Anaphylactic reaction, Immunosuppression, Urticaria, Hypersensitivity reaction

ENDOCRINE DISORDERS:
Syndrome of inappropriate antidiuretic hormone secretion (SIADH)

METABOLISM AND NUTRITION DISORDERS:
Tumor lysis syndrome, Metabolic acidosis, Hypokalemia, Hypocalcemia, Hypophosphatemia, Hyperglycemia, Polydipsia

PSYCHIATRIC DISORDERS:
Panic attack, Catatonia, Mania, Paranoia, Delusion, Delirium, Bradyphrenia, Mutism, Mental status change, Echolalia, Logorrhea, Perseveration, Amnesia

NERVOUS SYSTEM DISORDERS:
Convulsion*, Status epilepticus (convulsive and nonconvulsive), reversible posterior leukoencephalopathy syndrome, Leukoencephalopathy, Extrapyramidal disorder, Asterixis, Movement disorder, Polyneuropathy, Dysesthesia, Hypothesia, Paresthesia, Neuralgia, Gait disturbance, Fecal incontinence, Dysarthria

EYE DISORDERS:
Visual impairment, Vision blurred, Conjunctivitis, Eye irritation

EAR AND LABYRINTH DISORDERS: Deafness, Hypoacusis, Vertigo, Tinnitus

CARDIAC DISORDERS:
Cardiotoxicity*, Cardiac arrest*, Ventricular fibrillation*, Ventricular tachycardia*, Cardiogenic shock*, Myocardial infarction*, Cardiac failure*, Bundle branch block left, Bundle branch block right, Pericardial effusion, Myocardial hemorrhage, Angina pectoris, Left ventricular failure, Cardiomyopathy*, Congestive cardiomyopathy, Myocarditis*, Arrhythmia*, Pericarditis, Atrial fibrillation, Atrial flutter, Bradycardia, Supraventricular extrasystoles, Premature atrial contractions, Ventricular extrasystoles, Myocardial depression, Palpitations, Ejection fraction decreased*, Electrocardiogram ST-segment abnormal, Electrocardiogram T-wave inversion, Electrocardiogram QRS complex abnormal

VASCULAR DISORDERS:
Pulmonary embolism, Deep vein thrombosis, Capillary leak syndrome, Vasculitis, Hypertension, Flushing, Blood pressure decreased

RESPIRATORY, THORACIC, AND MEDIASTINAL DISORDERS:
Respiratory failure*, Acute respiratory distress syndrome*, Pulmonary hypertension*, Interstitial lung disease* as manifested by Pulmonary fibrosis*, Alveolitis allergic, Interstitial pneumonitis, Pneumonitis*, Pulmonary edema*, Pleural effusion, Bronchospasm, Dyspnea, Hypoxia, Cough
GASTROINTESTINAL DISORDERS:
Cecitis, Colitis, Enterocolitis, Pancreatitis, Ileus, Gastrointestinal hemorrhage, Mucosal ulceration, Constipation, Abdominal pain, Salivary hypersecretion

HEPATOBILIARY DISORDERS:
Hepatic failure*, Hepatitis fulminant*, Veno-occlusive liver disease, Portal vein thrombosis, Cytolytic hepatitis, Cholestasis

SKIN AND SUBCUTANEOUS TISSUE DISORDERS:
Toxic epidermal necrolysis, Stevens-Johnson syndrome, Palmar-plantar erythrodysesthesia syndrome, Radiation recall dermatitis, Skin necrosis, Facial swelling, Petechiae, Macular rash, Rash, Pruritus, Erythema, Skin hyperpigmentation, Hyperhidrosis, nail disorder

MUSCULOSKELETAL AND CONNECTIVE TISSUE DISORDER:
Rhabdomyolysis, Osteomalacia, Rickets, Growth retardation, Myalgia, Arthralgia, Pain in extremity, Muscle twitching

RENAL AND URINARY DISORDERS:
Fanconi syndrome, Tubulointerstitial nephritis, Nephrogenic diabetes insipidus, Phosphaturia, Aminoaciduria, Polyuria, Enuresis, Feeling of residual urine
Fatal outcomes from acute and chronic renal failure have been documented. REPRODUCTIVE SYSTEM AND BREAST DISORDERS:
Infertility, Ovarian failure, Premature menopause, Amenorrhea, Ovarian disorder, Ovulation disorder, Azoospermia, Oligospermia, Impairment of spermatogenesis, Blood estrogen decreased, Blood gonadotrophin increased

CONGENITAL, FAMILIAL AND GENETIC DISORDERS: Fetal growth retardation

GENERAL DISORDERS AND ADMINISTRATIVE SITE CONDITIONS:
Multi-organ failure*, General physical deterioration, Injection/Infusion site reactions including swelling, inflammation, pain, erythema, tenderness, pruritus; Chest pain, Edema, Mucosal inflammation, Pain, Pyrexia, Chills

* Including fatal outcomes

7 DRUG INTERACTIONS

Ifosfamide is a substrate for both CYP3A4 and CYP2B6.

7.1 Inducers of CYP3A4

CYP3A4 inducers (e.g., carbamazepine, phenytoin, fosphenytoin, phenobarbital, rifampin, St. John Wort) may increase the metabolism of ifosfamide to its active alkylating metabolites. CYP3A4 inducers may increase the formation of the neurotoxic/nephrotoxic ifosfamide metabolite, chloroacetaldehyde. Closely monitor patients taking ifosfamide with CYP3A4 inducers for toxicities and consider dose adjustment.

7.2 Inhibitors of CYP3A4

CYP3A4 inhibitors (e.g., ketoconazole, fluconazole, itraconazole, sorafenib, aprepitant, fosaprepitant, grapefruit, grapefruit juice) may decrease the metabolism of ifosfamide to its active alkylating metabolites, perhaps decreasing the effectiveness of ifosfamide treatment.

8 USE IN SPECIFIC POPULATIONS

8.1 Pregnancy

Pregnancy Category D [see Warnings and Precautions (5.8)].

Ifosfamide for Injection can cause fetal harm when administered to a pregnant woman. Fetal growth retardation and neonatal anemia have been reported following exposure to ifosfamide-containing chemotherapy regimens during pregnancy.

Animal studies indicate that ifosfamide is capable of causing gene mutations and chromosomal damage in vivo. In pregnant mice, resorptions increased and anomalies were present at day 19 after a 30 mg/m^2 dose of ifosfamide was administered on day 11 of gestation. Embryo-lethal effects were observed in rats following the administration of 54 mg/m^2 doses of ifosfamide from the 6th through the 15th day of gestation and embryotoxic effects were apparent after dams received 18 mg/m^2 doses over the same dosing period. Ifosfamide is embryotoxic to rabbits receiving 88 mg/m^2/day doses from the 6th through the 18th day after mating. The number of anomalies was also significantly increased over the control group.

Women should not become pregnant and men should not father a child during therapy with ifosfamide. Further, men should not father a child for up to 6 months after the end of therapy. If this drug is used during pregnancy, or if the patient becomes pregnant while taking this drug or after treatment, the patient should be apprised of the potential hazard to a fetus.

8.3 Nursing Mothers

Ifosfamide is excreted in breast milk. Because of the potential for serious adverse events and the tumorigenicity shown for ifosfamide in animal studies, a decision should be made whether to discontinue nursing or to discontinue the drug, taking into account the importance of the drug to the mother. Women must not breastfeed during treatment with ifosfamide.

8.4 Pediatric Use

Safety and effectiveness have not been established in pediatric patients.

8.5 Geriatric Use

In general, dose selection for an elderly patient should be cautious, reflecting the greater frequency of decreased hepatic, renal, or cardiac function, and of concomitant disease or other drug therapy.

A study of patients 40 to 71 years of age indicated that elimination half-life appears to increase with advancing age [see Pharmacokinetics (12.3)]. This apparent increase in half-life appeared to be related to increases in volume of distribution of ifosfamide with age. No significant changes in total plasma clearance or renal or non-renal clearance with age were reported.

Ifosfamide and its metabolites are known to be substantially excreted by the kidney, and the risk of toxic reactions to this drug may be greater in patients with impaired renal function. Because elderly patients are
more likely to have decreased renal function, care should be taken in dose selection, and it may be useful to monitor renal function.

8.6 Use in Patients with Renal Impairment

No formal studies were conducted in patients with renal impairment. Ifosfamide and its metabolites are known to be excreted by the kidneys and may accumulate in plasma with decreased renal function. Patients with renal impairment should be closely monitored for toxicity and dose reduction may be considered. Ifosfamide and its metabolites are dialyzable.

8.7 Use in Patients with Hepatic Impairment

No formal studies were conducted in patients with hepatic impairment. Ifosfamide is extensively metabolized in the liver and forms both efficacious and toxic metabolites. Ifosfamide for Injection should be given cautiously to patients with impaired hepatic function.

10 OVERDOSAGE

No specific antidote for Ifosfamide for Injection is known.

Patients who receive an overdose should be closely monitored for the development of toxicities. Serious consequences of overdosage include manifestations of dose-dependent toxicities such as CNS toxicity, nephrotoxicity, myelosuppression, and mucositis [see Warnings and Precautions (5)].
Management of overdosage would include general supportive measures to sustain the patient through any period of toxicity that might occur, including appropriate state-of-the-art treatment for any concurrent infection, myelosuppression, or other toxicity. Ifosfamide as well as ifosfamide metabolites are dialyzable.

Cystitis prophylaxis with mesna may be helpful in preventing or limiting urotoxic effects with overdose.

11 DESCRIPTION

Ifosfamide for Injection, USP single-dose vials for constitution and administration by intravenous infusion each contain 1 gram or 3 grams of sterile ifosfamide. Ifosfamide is a chemotherapeutic agent chemically related to the nitrogen mustards and a synthetic analog of cyclophosphamide. Ifosfamide is 3-(2-chloroethyl)-2-[(2-chloroethyl)amino]tetrahydro-2H-1,3,2 oxazaphosphorine 2-oxide. The molecular formula is C7 H15 Cl2 N2 O2 P and its molecular weight is 261.1. Ifosfamide is a white crystalline powder soluble in water. There are no excipients in the formulation. Each vial contains 1 gram or 3 grams of sterile ifosfamide alone.
Its structural formula is:

12 CLINICAL PHARMACOLOGY

12.1 Mechanism of Action

Ifosfamide is a prodrug that requires metabolic activation by hepatic cytochrome P450 isoenzymes to exert its cytotoxic activity. Activation occurs by hydroxylation at the ring carbon atom forming the unstable intermediate 4-hydroxyifosfamide and its ring-opened aldo tautomer, which decomposes to yield the cytotoxic and urotoxic compound acrolein and an alkylating isophosphoramide mustard as well as multiple other nontoxic products. The exact mechanism of action of ifosfamide has not been determined, but its cytotoxic action is primarily through DNA crosslinks caused by alkylation by the isophosphoramide mustard at guanine N-7 positions. The formation of inter- and intra-strand cross-links in the DNA results in cell death.

12.3 Pharmacokinetics

Ifosfamide exhibits dose-dependent pharmacokinetics in humans. At single doses of 3.8 to 5.0 g/m^2, the plasma concentrations decay biphasically and the mean terminal elimination half-life is about 15 hours. At doses of 1.6 to 2.4 g/m^2/day, the plasma decay is monoexponential and the terminal elimination half-life is about 7 hours.

Ifosfamide exhibits time-dependent pharmacokinetics in humans. Following intravenous administration of 1.5 g/m^2 over 0.5 hour once daily for 5 days to 15 patients with neoplastic disease, a decrease in the median elimination half-life from 7.2 hour on Day 1 to 4.6 hours on Day 5 occurred with a concomitant increase in the median clearance from 66 mL/min on Day 1 to 115 mL/min on Day 5. There was no significant change in the volume of distribution on Day 5 compared with Day 1.

Distribution
Ifosfamide volume of distribution (Vd) approximates the total body water volume, suggesting that distribution takes place with minimal tissue binding. Following intravenous administration of 1.5 g/m^2 over 0.5 hour once daily for 5 days to 15 patients with neoplastic disease, the median Vd of ifosfamide was 0.64
L/kg on Day 1 and 0.72 L/kg on Day 5. Ifosfamide shows little plasma protein binding. Ifosfamide and its active metabolites are extensively bound by red blood cells. Ifosfamide is not a substrate for P-glycoprotein.

Metabolism
Ifosfamide is extensively metabolized in humans through two metabolic pathways: ring oxidation (“activation”) to form the active metabolite, 4-hydroxy-ifosfamide and side-chain oxidation to form the inactive metabolites, 3-dechloro-ethylifosfamide or 2-dechloroethylifosfamide with liberation of the toxic metabolite, chloroacetaldehyde. Small quantities (nmol/mL) of ifosfamide mustard and 4-hydroxyifosfamide are detectable in human plasma. Metabolism of ifosfamide is required for the generation of the biologically active species and while metabolism is extensive, it is also quite variable among patients.

Excretion
After administration of doses of 5 g/m^2 of ^14C-labeled ifosfamide, from 70% to 86% of the dosed radioactivity was recovered in urine as metabolites, with about 61% of the dose excreted as parent compound. At doses of 1.6 to 2.4 g/m^2 only 12% to 18% of the dose was excreted in the urine as unchanged drug within 72 hours. Two different dechloroethylated derivatives of ifosfamide, 4-carboxyifosfamide, thiodiacetic acid and cysteine conjugates of chloroacetic acid have been identified as the major urinary metabolites of ifosfamide in humans and only small amounts of 4-hydroxyifosfamide and acrolein are present.
Pediatrics
Population PK analysis was performed on plasma data from 32 pediatric patients various malignant diseases aged between 1 and 18 years. Patients received a total of 45 courses of ifosfamide at doses of 1.2, 2.0 and 3.0 g/m^2 given intravenously over 1 or 3 hours on 1, 2, or 3 days. The mean±standard error population estimates for the initial clearance and volume of distribution of ifosfamide were 2.4±0.33 L/h/m^2 and 21±1.6 L/m^2 with an interindividual variability of 43% and 32%, respectively.

Effect of Age
A study of 20 patients between 40 to 71 years of age receiving 1.5 g/m^2 of ifosfamide daily for 3 or 5 days indicated that elimination half-life appears to increase with age. The elimination half-life increase appeared to be related to the increase in ifosfamide volume of distribution with age. No significant changes in total plasma clearance or renal clearance with age were reported.

13 NONCLINICAL TOXICOLOGY

13.1 Carcinogenesis, Mutagenesis, Impairment of Fertility

Ifosfamide has been shown to be carcinogenic in rats when administered by intraperitoneal injection at 6 mg/kg (37 mg/m^2, or about 3% of the daily human dose on a mg/m^2 basis) 3 times a week for 52 weeks. Female rats had a significantly higher incidence of uterine leiomyosarcomas and mammary fibroadenomas than vehicle controls.

The mutagenic potential of ifosfamide has been documented in bacterial systems in vitro and mammalian cells in vivo. In vivo, ifosfamide has induced mutagenic effects in mice and Drosophila melanogaster germ cells, and has induced a significant increase in dominant lethal mutations in male mice as well as recessive sex-linked lethal mutations in Drosophila.

Ifosfamide was administered to male and female beagle dogs at doses of 1.00 or 4.64 mg/kg/day (20 or 93 mg/m^2) orally 6 days a week for 26 weeks. Male dogs at 4.64 mg/kg (about 7.7% of the daily clinical dose on a mg/m^2 basis) had testicular atrophy with degeneration of the seminiferous tubular epithelium. In a second study, male and female rats were given 0, 25, 50, or 100 mg/kg (0, 150, 300, or 600 mg/m^2) ifosfamide intraperitoneally once every 3 weeks for 6 months. Decreased spermatogenesis was observed in most male rats given 100 mg/kg (about half the daily clinical dose on a mg/m^2 basis).

14 CLINICAL STUDIES

Patients with refractory testicular cancer (n=59) received a combination of ifosfamide, cisplatin, and either etoposide (VePesid) or vinblastine (VIP) as third-line therapy or later. The selection of etoposide or vinblastine ("V" in the VIP regimen) was guided by the therapeutic effect achieved with prior regimens. The contribution of ifosfamide to the VIP combination was determined in patients treated with cisplatin-etoposide prior to ifosfamide-cisplatin-etoposide or those who received cisplatin-vinblastine prior to ifosfamide-cisplatin-vinblastine.

A total of 59 patients received a third-line salvage regimen which consisted of ifosfamide 1.2 g/m^2/day intravenously on days 1 to 5, cisplatin 20 mg/m^2/day intravenously on days 1 to 5, and either etoposide 75 mg/m2/day intravenously on days 1 to 5 or vinblastine 0.22 mg/kg intravenously on day 1. Efficacy results with the VIP regimen were compared to data pooled from six single agent phase II trials conducted between August 1980 and October 1985 including a total of 90 patients of whom 65 were eligible as controls of this study. Twenty-three patients in the VIP regimen became free of disease with VIP alone or VIP plus surgery, whereas a single patient in the historical control group achieved complete response. The median survival time exceeded two years in the VIP group versus less than one year in the control group.

Performance status ≥ 80, embryonal carcinoma and minimal disease were favorable prognostic factors for survival. In all prognostic categories, the difference between VIP and historical controls remained highly significant.

Table 1. Efficacy Results

 | Number. (%) of Patients
 | VIP | Control | p-value
Total Patients | 59 (100) | 65 (100)
Disease-free | 23 (39) | 1 (2) | < 0.001
Chemotherapy alone | 15 (25) | 1 (2) | < 0.001
Chemotherapy plus surgery | 8 (14) | 0
Overall Response | 32 (54) | 2 (3) | < 0.001
Time to progression (weeks)
Median | 19 | 4 | < 0.001a
Range | 1 – 205+ | 1 – 29
Disease-free interval (weeks)
Median | 114 | 29
Range | 13 – 205+ | --
Survival (weeks)
Median | 53 | 10 | < 0.001a
Range | 1 – 205+ | 1 – 123+

a: Gehan-Breslow and Mantel-Cox tests

In a study, 50 fully evaluable patients with germ cell testicular cancer were treated with Ifosfamide for Injection in combination with cisplatin and either vinblastine or etoposide after failing (47 of 50 patients) at least two prior chemotherapy regimens consisting of cisplatin/vinblastine/bleomycin, (PVB), cisplatin/vinblastine/actinomycin D/bleomycin/cyclophosphamide, (VAB6), or the combination of cisplatin and etoposide. Patients were selected for remaining cisplatin sensitivity because they had previously responded to a cisplatin containing regimen and had not progressed while on the cisplatin containing regimen or within 3 weeks of stopping it. Patients served as their own control based on the premise that long term complete responses could not be achieved by retreatment with a regimen to which they had previously responded and subsequently relapsed.

Ten of 50 fully evaluable patients were still alive 2 to 5 years after treatment. Four of the 10 long term survivors were rendered free of cancer by surgical resection after treatment with the ifosfamide regimen; median survival for the entire group of 50 fully evaluable patients was 53 weeks.

15 REFERENCES

1. NIOSH Alert: Preventing occupational exposures to antineoplastic and other hazardous drugs in healthcare settings. 2004. U.S. Department of Health and Human Services, Public Health Service, Centers for Disease Control and Prevention, National Institute for Occupational Safety and Health, DHHS (NIOSH) Publication No. 2004-165.
2. OSHA Technical Manual, TED 1-0.15A, Section VI: Chapter 2. Controlling occupational exposure to hazardous drugs. OSHA, 1999. http://www.osha.gov/dts/osta/otm/otm_vi/otm_vi_2.html
3. American Society of Health-System Pharmacists. ASHP guidelines on handling hazardous drugs. Am J Health-Syst Pharm. 2006;63:1172-1193.
4. Polovich M, White JM, Kelleher LO, (eds.) 2005. Chemotherapy and biotherapy guidelines and recommendations for practice. (2nd ed.) Pittsburgh, PA: Oncology Nursing Society.

16 HOW SUPPLIED/STORAGE AND HANDLING

Ifosfamide for Injection, USP, is available in single-dose vials as follows:

Product No. | NDC No.
104210 | 63323-142-10 | 1 gram single dose vial, packaged individually.
104300 | 63323-143-00 | 3 grams single dose vial, packaged individually.

The container closure is not made with natural rubber latex.

Store at controlled room temperature 20°C to 25°C (68°F to 77°F). Protect from temperatures above 30°C (86°F).

Exercise caution when handling Ifosfamide for Injection. The handling and preparation of ifosfamide should always be in accordance with current guidelines on safe handling of cytotoxic agents. Several guidelines on this subject have been published.^1-4 Skin reactions associated with accidental exposure to Ifosfamide for Injection may occur. To minimize the risk of dermal exposure, always wear impervious gloves when handling vials and solutions containing Ifosfamide for Injection. If Ifosfamide for Injection solution contacts the skin or mucosa, immediately wash the skin thoroughly with soap and water or rinse the mucosa with copious amounts of water.

17 PATIENT COUNSELING INFORMATION

Inform patients of the risks associated with the use of Ifosfamide for Injection as well as the plan for regular blood monitoring during therapy.
Specifically inform patients of the following:

- Treatment with ifosfamide may cause myelosuppression which can be severe and lead to fatal outcome. Significant suppression of immune responses can also occur which can lead to severe infections. Latent infections can be reactivated. Patients should report fever or other symptoms of an infection.
- The risk of bleeding and anemia.
- The risk of CNS toxicity and other neurotoxic effects with fatal outcome.
- The risk of bladder and kidney toxicity. Patients should be aware of the need to increase fluid intake and frequent voiding to prevent accumulation in the bladder.
- The risk of cardiotoxicity and fatal outcome. Patients should report preexisting cardiac disease.
- The risk of pulmonary toxicity leading to respiratory failure with fatal outcome.
- The risk of secondary malignancies due to therapy.
- The risk of veno-occlusive liver disease.
- The potential hazard to a fetus if a patient becomes pregnant or fathers a child during therapy and for up to 6 months after therapy. Effective methods of contraception should be used during therapy and for up to 6 months after therapy.
- The potential for serious adverse reactions and tumorigenicity when children are breastfed during therapy.
- The risk of amenorrhea, premature menopause, and sterility.
- The risk of alopecia, wound healing, and other serious skin and subcutaneous tissue disorders.
- Therapy may cause gastrointestinal disorders and alcohol may increase nausea and vomiting.
- The risk of stomatitis and the importance of proper oral hygiene.
- The risk of eye disorders such as visual impairment, blurred vision, and eye irritation.
- The risk of ear and labyrinth disorders such as deafness, vertigo, and tinnitus.

The brand names mentioned in this document are the trademarks of their respective owners.

www.fresenius-kabi.com/us
45929D
Revised: December 2017

PACKAGE LABEL

PACKAGE LABEL - PRINCIPAL DISPLAY - Ifosfamide 1 g Vial Label

Ifosfamide
for Injection, USP

1 gram per vial

For intravenous use.

Single Dose Vial

Rx only

PACKAGE LABEL - PRINCIPAL DISPLAY - Ifosfamide 1 g Vial Carton Panel

Ifosfamide
for Injection, USP

1 gram per vial

For intravenous use.

Rx only
Single Dose Vial